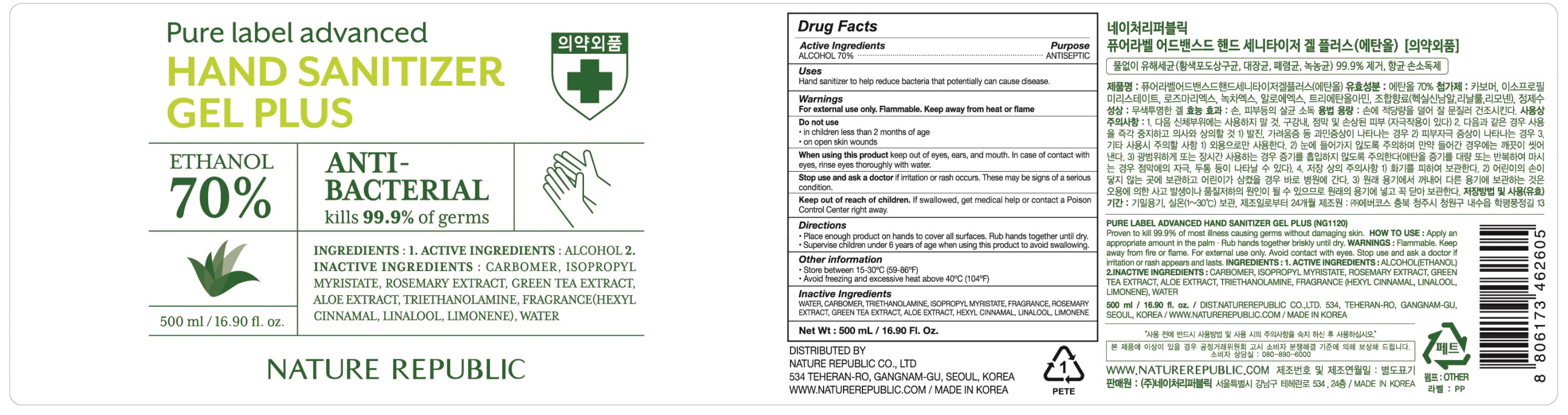 DRUG LABEL: Pure label advanced hand sanitizer ge l plus
NDC: 51346-531 | Form: GEL
Manufacturer: NATURE REPUBLIC CO., LTD.
Category: otc | Type: HUMAN OTC DRUG LABEL
Date: 20200426

ACTIVE INGREDIENTS: ALCOHOL 350 mL/500 mL
INACTIVE INGREDIENTS: Water; CARBOMER HOMOPOLYMER, UNSPECIFIED TYPE; TROLAMINE; Isopropyl myristate; GREEN TEA LEAF; ALOE; .ALPHA.-HEXYLCINNAMALDEHYDE; LINALOOL, (+/-)-; LIMONENE, (+)-

ACTIVE INGREDIENT

Active Ingredient: ALCOHOL 70%

INACTIVE INGREDIENT

Inactive ingredients:

Water, Carbomer, Triethanolamine, Isopropyl myristate, Fragrance, Rosemary Extract, Green Tea Extract, Aloe Extract, Hexyl Cinnamal, Linalool, Limonene

PURPOSE

Purpose: ANTISEPTIC

WARNINGS

For external use only. Flammable. Keep away from heat or flame
--------------------------------------------------------------------------------------------------------
Do not use
• in children less than 2 months of age
• on open skin wounds
--------------------------------------------------------------------------------------------------------
When using this product keep out of eyes, ears, and mouth. In case of contact with eyes, rinse eyes thoroughly with water.
--------------------------------------------------------------------------------------------------------
Stop use and ask a doctor if irritation or rash occurs. These may be signs of a serious condition.

Keep out of reach of children. If swallowed, get medical help or contact a Poison Control Center right away.

Uses

Hand sanitizer to help reduce bacteria that potentially can cause disease.

Directions

• Place enough product on hands to cover all surfaces. Rub hands together until dry.
• Supervise children under 6 years of age when using this product to avoid swallowing.

Other information

• Store between 15-30C (59-86F)
• Avoid freezing and excessive heat above 40C (104F)